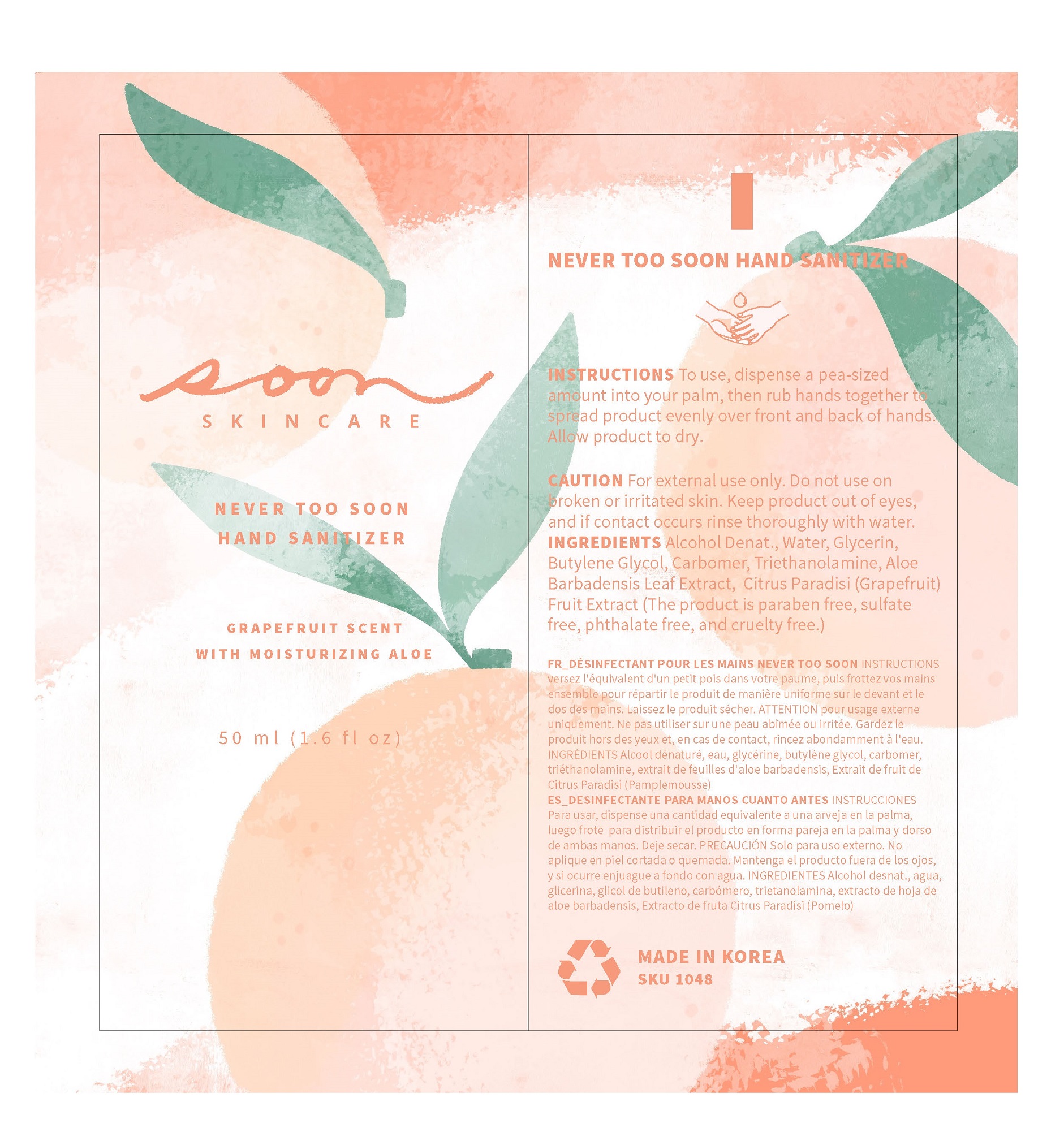 DRUG LABEL: NEVER TOO SOON HAND SANITIZER
NDC: 79615-0001 | Form: GEL
Manufacturer: Y Nature Co Ltd
Category: otc | Type: HUMAN OTC DRUG LABEL
Date: 20200711

ACTIVE INGREDIENTS: ALCOHOL 65 mL/100 mL
INACTIVE INGREDIENTS: TROLAMINE; BUTYLENE GLYCOL; CARBOMER 940; GLYCERIN; ALOE VERA LEAF; GRAPEFRUIT OIL

Active Ingredient(s)

alcohol

Purpose

hand sanitizer

Use

 Hand sanitizing to help reduce bacteria on the skin

Warnings

For external use only.
Flammable, keep away from fire or flame.
When using this product, avoid contact with the eyes. In case of contact, rinse eyes thoroughly with water.
Stop use and ask a doctor if irritation or redness appears and lasts.

 Keep out of reach of children. If swallowed, get medical help or contact a Poison Control Center immediately.

Directions

for external use only

INACTIVE INGREDIENT

Water
Glycerin
Butylene Glycol
Carbomer
Triethanolamine
Aloe Barbadensis Leaf Extract
Citrus Paradisi (Grapefruit) Fruit Extract